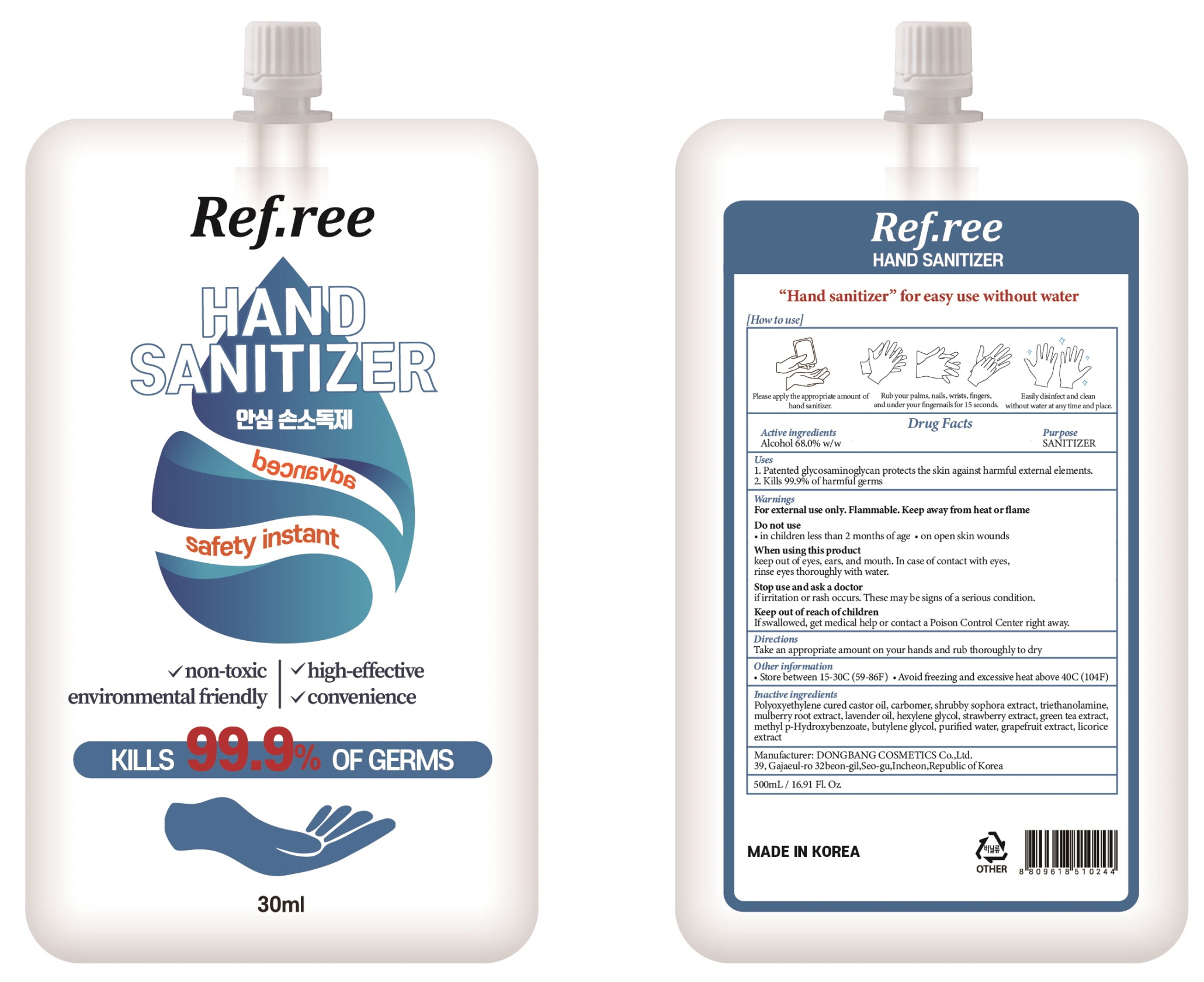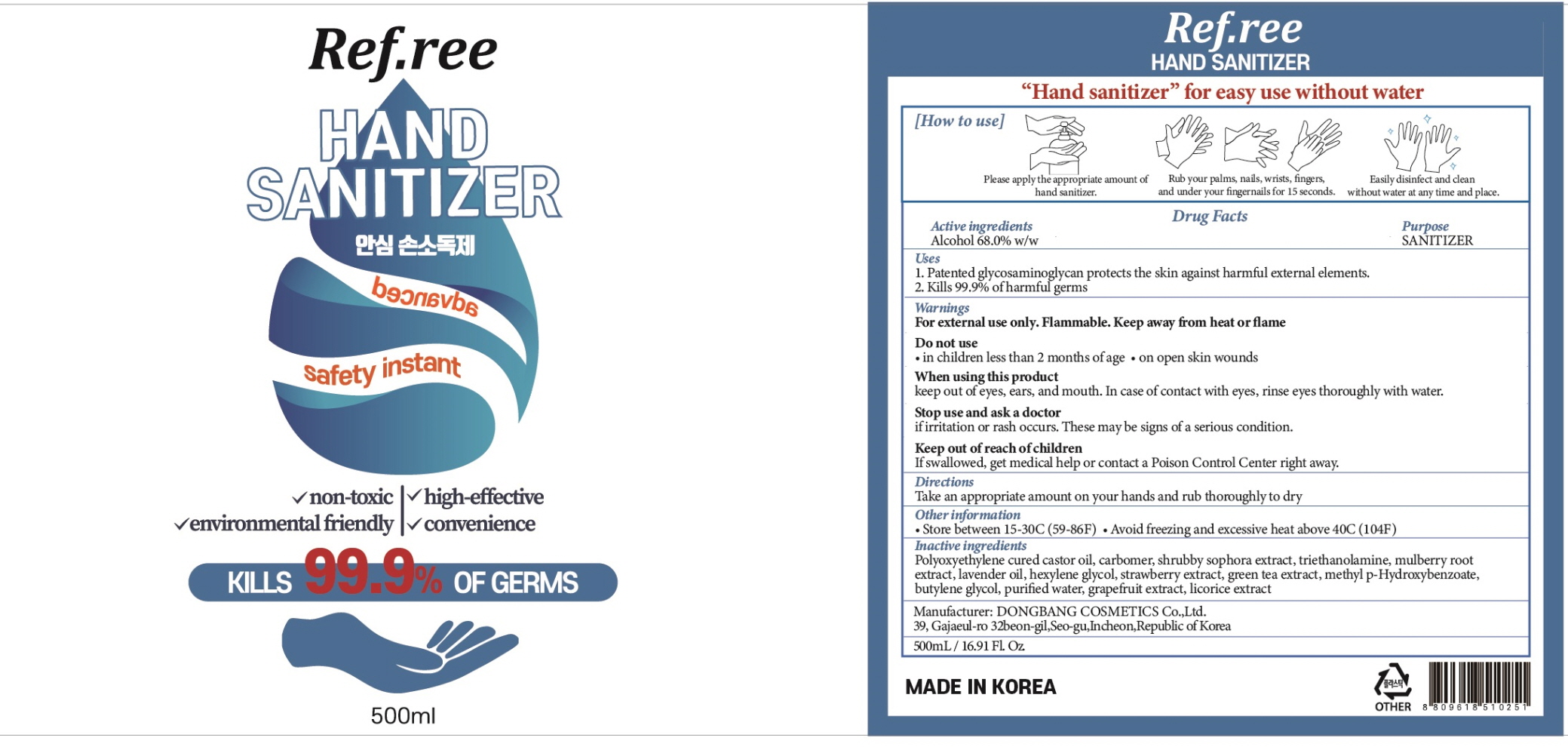 DRUG LABEL: REFREE HAND SANITIZER
NDC: 74002-5040 | Form: GEL
Manufacturer: DONGBANGCOSMETICS CO.,LTD
Category: otc | Type: HUMAN OTC DRUG LABEL
Date: 20200418

ACTIVE INGREDIENTS: ALCOHOL 68 g/100 mL
INACTIVE INGREDIENTS: Water; CARBOMER HOMOPOLYMER, UNSPECIFIED TYPE; TROLAMINE; lavender oil; hexylene glycol; STRAWBERRY SEED OIL; GREEN TEA LEAF; Butylene Glycol; GRAPEFRUIT OIL

ACTIVE INGREDIENT

Active ingredients: ALCOHOL 68.0% w/w

INACTIVE INGREDIENT

Inactive Ingredients:

Polyoxyethylene cured castor oil, carbomer, shrubby sophora extract, triethanolamine, mulberry root extract, lavender oil, hexylene glycol, strawberry extract, green tea extract, methyl p-Hydroxybenzoate, butylene glycol, purified water, grapefruit extract, licorice extract

PURPOSE

Purpose: SANITIZER

WARNINGS

For external use only. Flammable. Keep away from heat or flame
--------------------------------------------------------------------------------------------------------
Do not use
• in children less than 2 months of age
• on open skin wounds
--------------------------------------------------------------------------------------------------------
When using this product keep out of eyes, ears, and mouth. In case of contact with eyes, rinse eyes thoroughly with water.
--------------------------------------------------------------------------------------------------------
Stop use and ask a doctor if irritation or rash occurs. These may be signs of a serious condition.

Keep out of reach of children. If swallowed, get medical help or contact a Poison Control Center right away.

Uses

1. Patented glycosaminoglycan protects the skin against harmful external elements.
2. Kills 99.9% of harmful germs

Directions

Take an appropriate amount on your hands and rub thoroughly to dry.

Other Information

• Store between 15-30C (59-86F)
• Avoid freezing and excessive heat above 40C (104F)